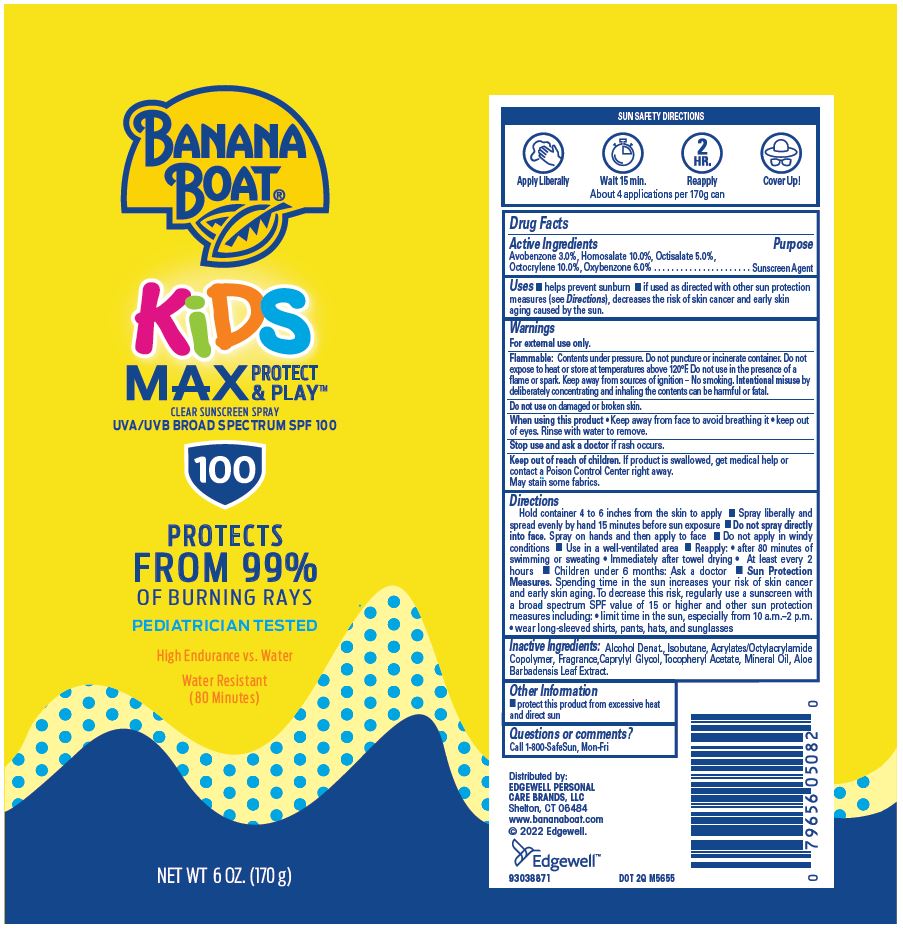 DRUG LABEL: Banana Boat
NDC: 63354-129 | Form: SPRAY
Manufacturer: Edgewell Personal Care Brands, LLC
Category: otc | Type: HUMAN OTC DRUG LABEL
Date: 20240223

ACTIVE INGREDIENTS: OCTISALATE 5 g/100 g; OCTOCRYLENE 10 g/100 g; OXYBENZONE 6 g/100 g; AVOBENZONE 3 g/100 g; HOMOSALATE 10 g/100 g
INACTIVE INGREDIENTS: ALCOHOL; ALOE VERA LEAF; ISOBUTANE; CAPRYLYL GLYCOL; ALPHA-TOCOPHEROL ACETATE; MINERAL OIL

Acitve Ingredients

Avobenzone 3.0%, Homosalate 10.0%, Octisalate 5.0%, Octocrylene 10.0%, Oxybenzone 6.0%

Purpose

Sunscreen

Uses

- Helps prevent Sunburn
- If used as directed with other sun protection measures (see Directions), decreases the risk of cancer and early skin aging caused by the sun

Warnings

For external use only

Flammable. Contents under pressure. Do not puncture or incinerate container. Do not expose to heat or store at temperatures above 120ºF. Do not use in the presence of a flame or spark. Keep away from sources of ignition - No smoking. Intentional misuse by deliberately concentrating and inhaling the contents can be harmful or fatal.

May stain some fabrics

Do not use

on damaged or broken skin

When using this product

Keep away from face to avoid breathing it.

Keep out of eyes. Rinse with water to remove.

Stop use and ask a doctor

if rash occurs

Keep out of reach of children

If product is swallowed, get medical help or contact a Poison Control Center right away.

Directions

• Hold container 4 to 6 inches from the skin to apply • Spray liberally and spread evenly by hand 15 minutes before sun exposure • Do not spray directly into face. Spray on hands and then apply to face. • Do not apply in windy conditions • Use in a well-ventilated area • Reapply: •after 80 minutes of swimming or sweating • immediately after towel drying • at least every 2 hours • Children under 6 months: Ask a doctor • Sun Protection Measures. Spending time in the sun increases your risk of skin cancer and early skin aging. To decrease this risk, regularly use a sunscreen with a Broad Spectrum SPF value of 15 or higher and other sun protection measures including: • limit time in the sun, especially from 10 a.m. - 2 p.m., • wear long-sleeved shirts, pants, hats, and sunglasses.

Inactive Ingredients

Alcohol Denat., Isobutane, Acrylates/Octylacrylamide Copolymer, Fragrance, Caprylyl Glycol, Tocopheryl Acetate, Mineral Oil, Aloe Barbadensis Leaf Extract.

Other Information

Protect this product from excessive heat and direct sun

Questions or Comments?

Call 1-800-SAFESUN, Mon-Fri

Principal Display Panel

BANANA
BOAT®
KiDS
MAX PROTECT & PLAY™
CLEAR SUNSCREEN SPRAY
UVA/UVB BROAD SPECTRUM SPF 100
100
PROTECTS
FROM 99%
OF BURNING RAYS
PEDIATRICIAN TESTED
High Endurance vs. Water
Water Resistant
(80 Minutes)
NET WT 6 OZ. (170 g)